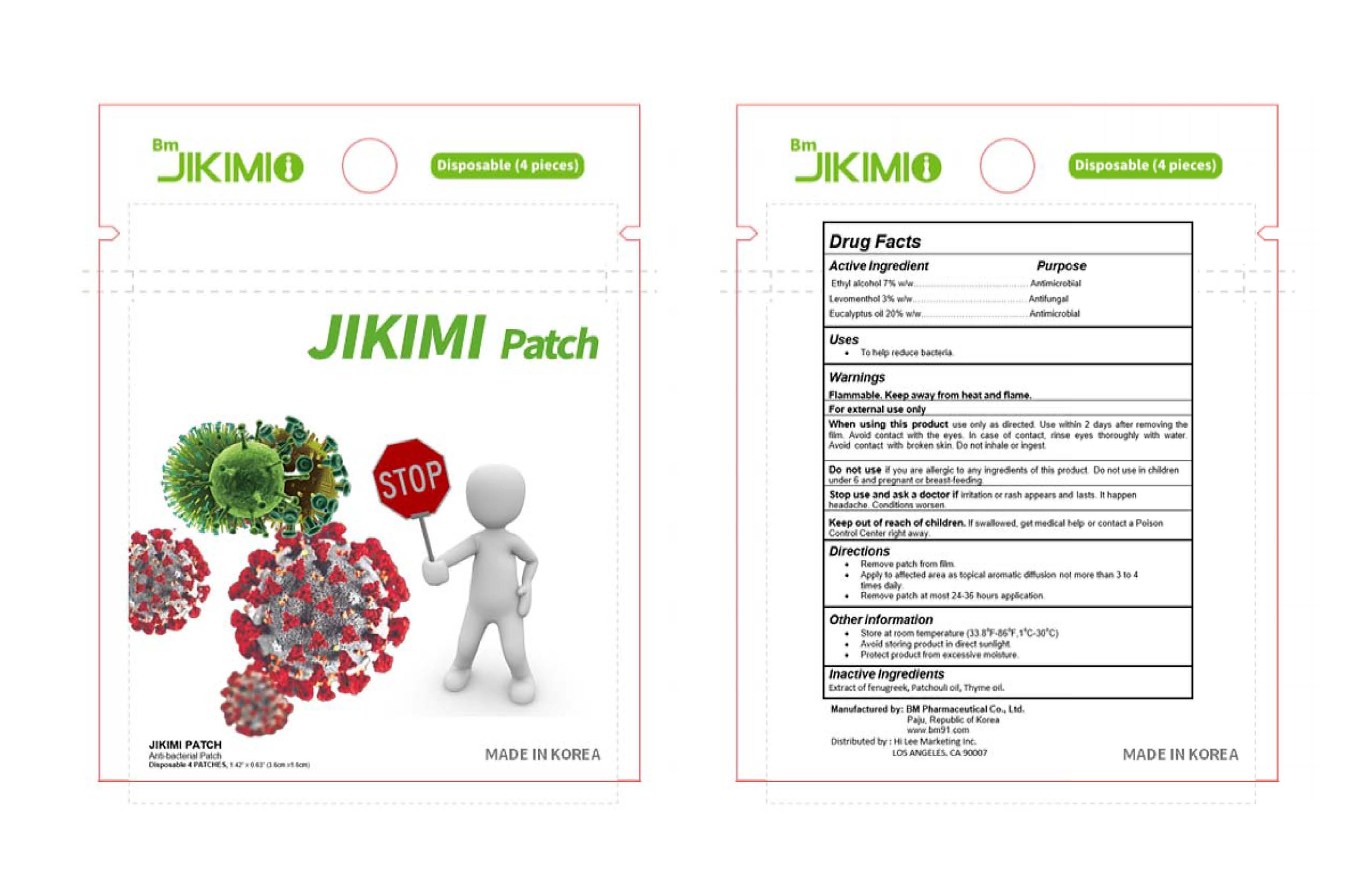 DRUG LABEL: Jikimi Patch
NDC: 76614-100 | Form: PATCH
Manufacturer: BM Pharmaceutical Co., Ltd.
Category: otc | Type: HUMAN OTC DRUG LABEL
Date: 20200505

ACTIVE INGREDIENTS: LEVOMENTHOL 0.03 1/1 1; ALCOHOL 0.07 1/1 1; EUCALYPTUS OIL 0.2 1/1 1
INACTIVE INGREDIENTS: FENUGREEK SEED OIL; POGOSTEMON CABLIN LEAF OIL; THYME OIL

Active Ingredient(s)

Ethyl alcohol 7% w/w………………………...………. Antimicrobial

Levomenthol 3% w/w………………………...………. Antifungal

Eucalyptus oil 20% w/w…………………………...…. Antimicrobial

Purpose

To help reduce bacteria.

Use

Apply to affected area as topical aromatic diffusion.

Warnings

For external use only. Flammable. Keep away from heat or flame

- Do not use if you are allergic to any ingredients of this product.
- Do not use in children under 6 and pregnant or breast-feeding.

When using this product use only as directed. Use within 2 days after removing the film. Avoid contact with the eyes. In case of contact, rinse eyes thoroughly with water. Avoid contact with broken skin. Do not inhale or ingest.

Stop use and ask a doctor if irritation or rash appears and lasts. It happen headache. Conditions worsen.

Keep out of reach of children. If swallowed, get medical help or contact a Poison Control Center right away.

Directions

Remove patch from film.
Apply to affected area as topical aromatic diffusion not more than 3 to 4 times daily.

Remove patch at most 24-36 hours application.

Other information

- Store at room temperature between 1-30oC (33.8-86oF).
- Avoid storing product in direct sunlight.
- Protect product from excessive moisture.

Inactive ingredients

Extract of fenugreek, Patchouli oil, Thyme oil.